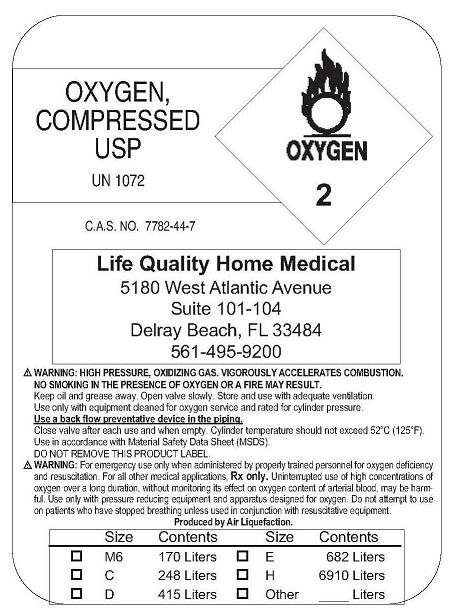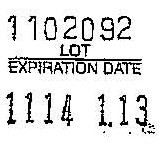 DRUG LABEL: Oxygen
NDC: 64481-0001 | Form: GAS
Manufacturer: Life Quality Home Healthcare, Inc. 
Category: prescription | Type: HUMAN PRESCRIPTION DRUG LABEL
Date: 20091104

ACTIVE INGREDIENTS: Oxygen 99 L/100 L

Oxygen

Principal for Oxygen Product

Oxygen Label

Lot Sticker